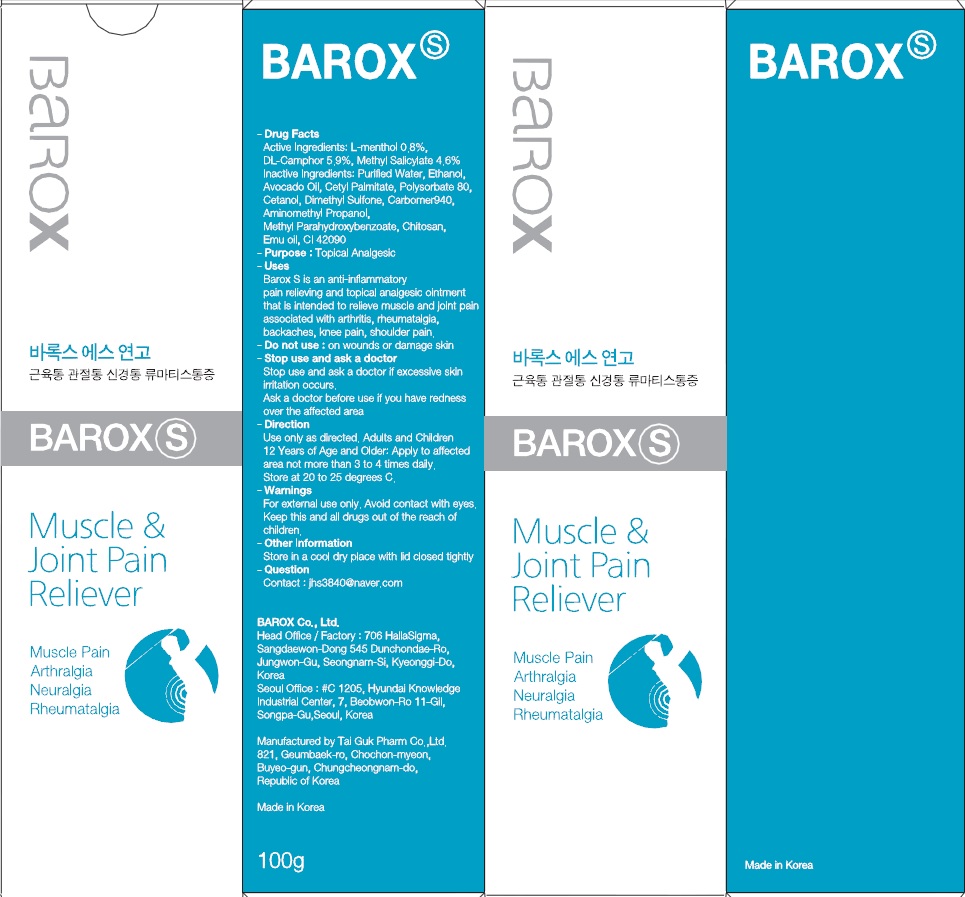 DRUG LABEL: BAROX
NDC: 55692-150 | Form: GEL
Manufacturer: Barox Co., Ltd.
Category: otc | Type: HUMAN OTC DRUG LABEL
Date: 20171116

ACTIVE INGREDIENTS: CAMPHOR (SYNTHETIC) 5.90 g/100 g; METHYL SALICYLATE 4.60 g/100 g; MENTHOL 0.80 g/100 g
INACTIVE INGREDIENTS: Water; AVOCADO OIL

ACTIVE INGREDIENT

Active ingredients: L-menthol 0.8%, DL-Camphor 5.9%, Methyl Salicylate 4.6%

INACTIVE INGREDIENT

Inactive Ingredients: Purified Water, Ethanol, Avocado Oil, Cetyl Palmitate, Polysorbate 80, Cetanol, Dimethyl Sulfone, Carbomer940, Aminomethyl Propanol, Methyl Parahydroxybenzoate, Chitosan, Emu oil, CI 42090

PURPOSE

Purpose: Topical Analgesic

WARNINGS

For external use only. Avoid contact with eyes. Keep this and all drugs out of the reach of children.

KEEP OUT OF REACH OF CHILDREN

Keep this and all drugs out of the reach of children.

Uses

Barox S is an anti-inflammatory pain relieving and topical analgesic ointment that is intended to relieve muscle and joint pain associated with arthritis, rheumatalgia, backaches, knee pain, shoulder pain.

Direction

Use only as directed. Adults and Children 12 Years of Age and Older: Apply to affected area not more than 3 to 4 times daily.

DESCRIPTION

- Do not use : on wounds or damage skin

- Stop use and ask a doctor:Stop use and ask a doctor if excessive skin irritation occurs. Ask a doctor before use if you have redness over the affected area

- Other Information : Store in a cool dry place with lid closed tightly

- Question Contact : jhs3840@naver.com